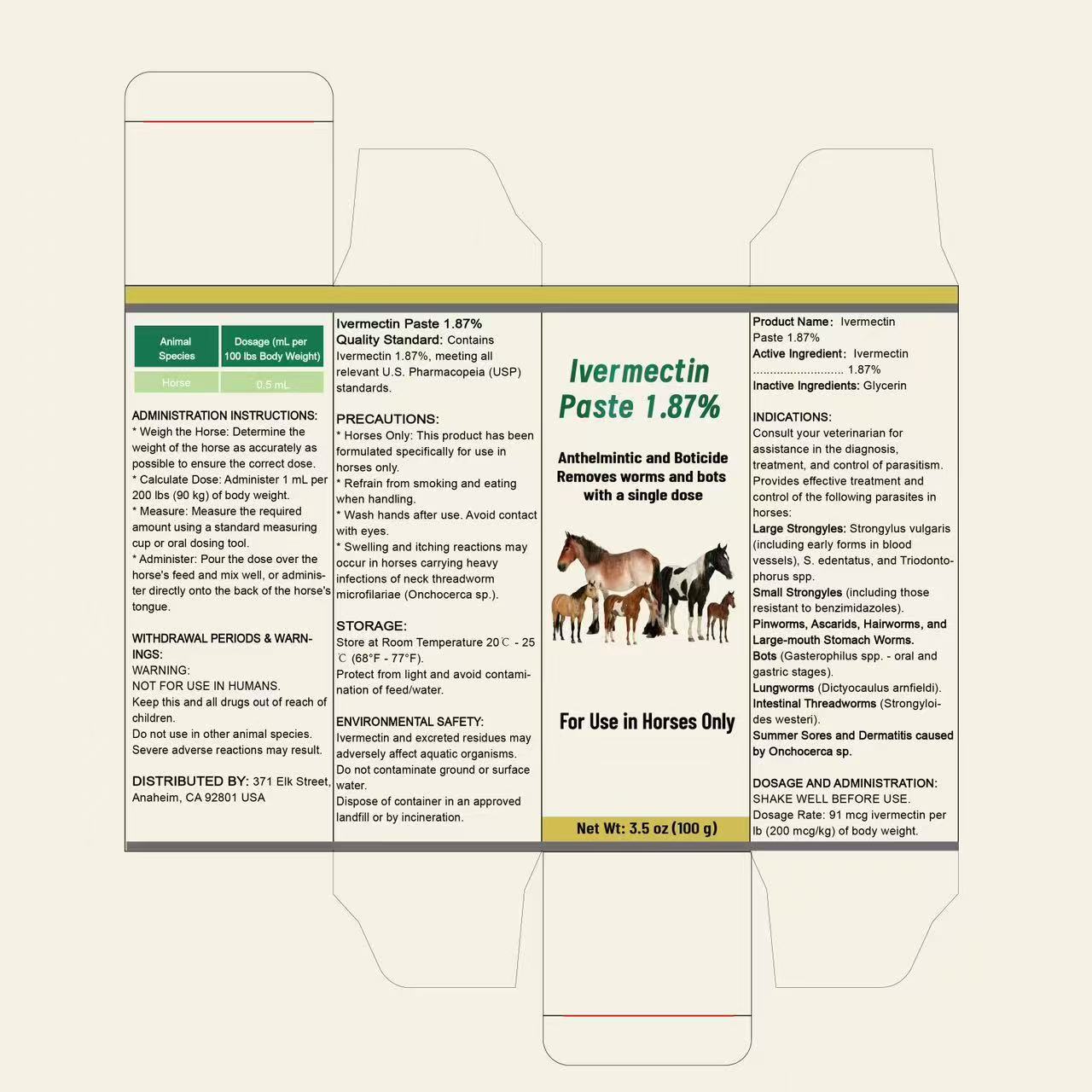 DRUG LABEL: Ivermectin
NDC: 87276-260 | Form: PASTE
Manufacturer: Shenzhen Zhenshangzekai Technology Co, Ltd.
Category: otc | Type: HUMAN OTC DRUG LABEL
Date: 20251217

ACTIVE INGREDIENTS: IVERMECTIN 1.87 g/100 g
INACTIVE INGREDIENTS: GLYCERIN

ACTIVE INGREDIENT

lvermectin

ASK DOCTOR

Consult your veterinarian for assistance in the diagnosis, treatment, and control of parasitism. Provides effective treatment and control of the following parasites in horses:

DOSAGE AND ADMINISTRATION

SHAKE WELL BEFORE USE

Dosage Rate: 91 mcg ivermectin per Ib (200 mcg/kg) of body weight.

ADMINISTRATION

* Weigh the Horse: Determine the weight of the horse as accurately as possible to ensure the correct dose.

*Calculate Dose: Administer 1 mL per 200 lbs (90 kg) of body weight.

*Measure: Measure the required amount using a standard measuring cup or oral dosing tool.

*Administer: Pour the dose over the horse's feed and mix well or adminiser directly onto the back of the horse's tongue.

WARNINGS

Horses Only: This product has been formulated specifically for use in horses only.

Refrain from smoking and eating when handling.

Wash hands after use. Avoid contact with eyes.

Swelling and itching reactions may occur in horses carrying heavy infections of neck thread worm microfilariae (Onchocerca sp.).

INACTIVE INGREDIENT

Glycerin

INDICATIONS AND USAGE

Consult your veterinarian for assistance in the diagnosis treatment, and control of parasitism. Provides effective treatment and control of the following parasites in horses:

Large Strongyles: Strongylus vulgaris(including early forms in blood vessels),S.edentatus, and Triodonto-phorus spp.

Small Strongyles (including those resistant to benzimidazoles)

Pinworms, Ascarids, Hairworms, and

Large-mouth Stomach Worms.Bots (Gasterophilus spp.-oral andgastric stages).

Lungworms (Dictyocaulus arnfieldi)Intestinal Threadworms (Strongyloi-des westeri).

Summer Sores and Dermatitis causedby Onchocerca sp.

Keep out reach of children

PURPOSE

Anthelmintic and Boticide

Removes worms and bots